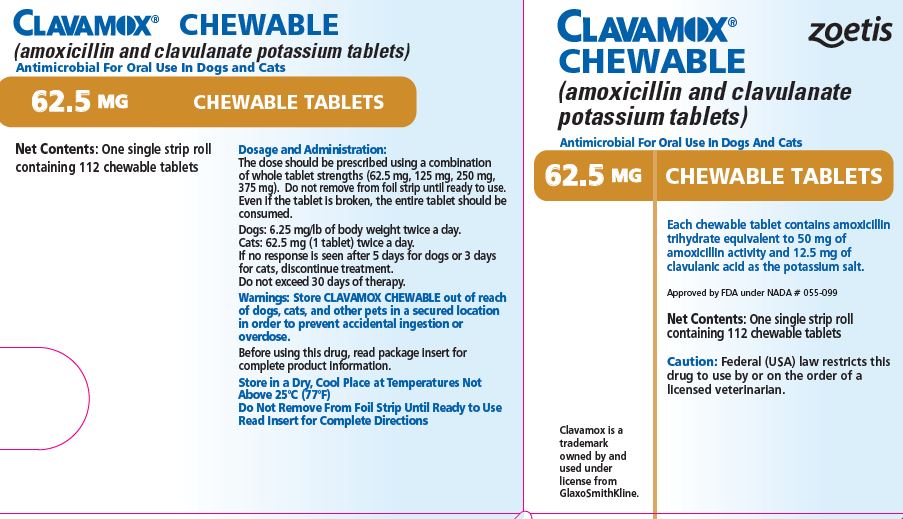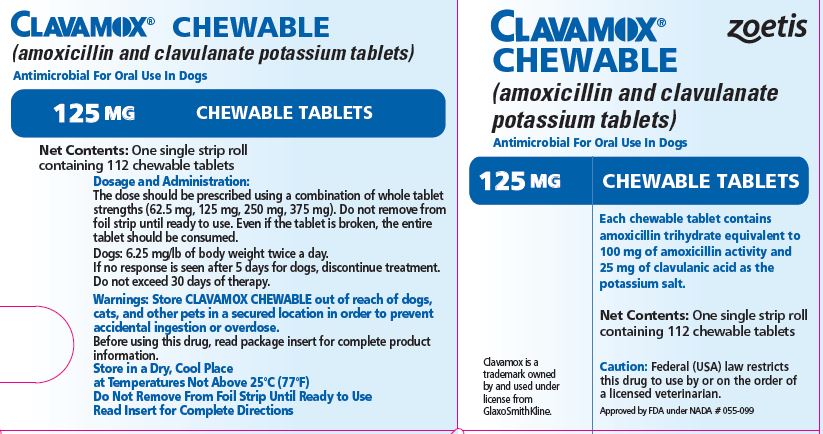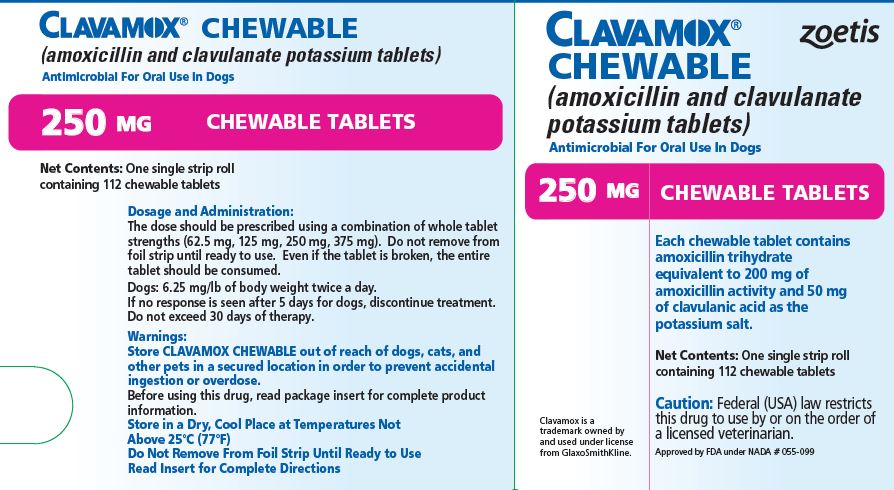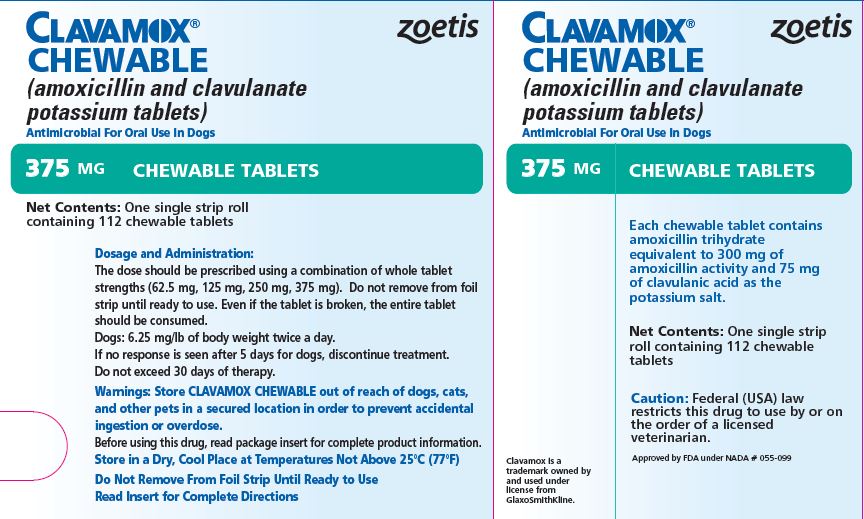 DRUG LABEL: Clavamox
NDC: 54771-1023 | Form: TABLET, CHEWABLE
Manufacturer: Zoetis Inc.
Category: animal | Type: PRESCRIPTION ANIMAL DRUG LABEL
Date: 20241114

ACTIVE INGREDIENTS: AMOXICILLIN 50 mg/1 1; CLAVULANATE POTASSIUM 12.5 mg/1 1

CLAVAMOX® CHEWABLE

CLAVAMOX® CHEWABLE
(amoxicillin and clavulanate potassium tablets)

Chewable Tablets

Antimicrobial For Oral Use In Dogs And Cats

CAUTION

Federal (USA) law restricts this drug to use by or on the order of a licensed veterinarian.

DESCRIPTION

CLAVAMOX CHEWABLE Tablet (amoxicillin and clavulanate potassium tablets) is an orally administered formulation comprised of the broad-spectrum antibiotic Amoxi® (amoxicillin trihydrate) and the β-lactamase inhibitor, clavulanate potassium (the potassium salt of clavulanic acid).

Amoxicillin trihydrate is a semisynthetic antibiotic with a broad spectrum of bactericidal activity against many gram-positive and gram-negative, aerobic and anaerobic microorganisms. It does not resist destruction by β-lactamases; therefore, it is not effective against β-lactamase-producing bacteria. Chemically, it is D(-)-α-amino-p-hydroxybenzyl penicillin trihydrate.

Clavulanic acid, an inhibitor of β-lactamase enzymes, is produced by the fermentation of Streptomyces clavuligerus. Clavulanic acid by itself has only weak antibacterial activity. Chemically, clavulanate potassium is potassium z-(3R,5R)-2-β-hydroxyethylidene clavam-3-carboxylate.

INDICATIONS

CLAVAMOX CHEWABLE Tablets are indicated in the treatment of:

Dogs: Skin and soft tissue infections such as wounds, abscesses, cellulitis, superficial/juvenile and deep pyoderma due to susceptible strains of the following organisms: β-lactamase-producing Staphylococcus aureus, non-β-lactamase-producing Staphylococcus aureus, Staphylococcus spp., Streptococcus spp., and E. coli.

Periodontal infections due to susceptible strains of both aerobic and anaerobic bacteria. CLAVAMOX CHEWABLE has been shown to be clinically effective for treating cases of canine periodontal disease.

Cats: Skin and soft tissue infections such as wounds, abscesses, and cellulitis/dermatitis due to susceptible strains of the following organisms: β-lactamase-producing Staphylococcus aureus, non-β-lactamase-producing Staphylococcus aureus, Staphylococcus spp., Streptococcus spp., E. coli, and Pasteurella spp.

Urinary tract infections (cystitis) due to susceptible strains of E. coli.

Therapy may be initiated with CLAVAMOX CHEWABLE prior to obtaining results from bacteriological and susceptibility studies. A culture should be obtained prior to treatment to determine susceptibility of the organisms to CLAVAMOX. Following determination of susceptibility results and clinical response to medication, therapy may be reevaluated.

DOSAGE AND ADMINISTRATION:

The dose should be prescribed using a combination of whole tablet strengths (62.5 mg, 125 mg, 250 mg, 375 mg). Do not remove from foil strip until ready to use. Even if the tablet is broken, the entire tablet should be consumed.

Dogs

The recommended dosage of CLAVAMOX CHEWABLE Tablet is 6.25 mg/lb of body weight twice a day.

Skin and soft tissue infections such as abscesses, cellulitis, wounds, superficial/juvenile pyoderma, and periodontal infections should be treated for 5-7 days or for 48 hours after all symptoms have subsided.

If no response is seen after 5 days of treatment, therapy should be discontinued and the case reevaluated. Deep pyoderma may require treatment for 21 days; the maximum duration of treatment should not exceed 30 days.

Cats

The recommended dosage of CLAVAMOX CHEWABLE Tablet is 62.5 mg twice a day.

Skin and soft tissue infections such as abscesses and cellulitis/dermatitis should be treated for 5-7 days or for 48 hours after all symptoms have subsided, not to exceed 30 days. If no response is seen after 3 days of treatment, therapy should be discontinued and the case reevaluated.

Urinary tract infections may require treatment for 10-14 days or longer. The maximum duration of treatment should not exceed 30 days.

CONTRAINDICATIONS

The use of this drug is contraindicated in animals with a history of allergic reaction to any of the penicillins or cephalosporins.

WARNINGS

Store CLAVAMOX CHEWABLE out of reach of dogs, cats, and other pets in a secured location in order to prevent accidental ingestion or overdose.

HUMAN WARNINGS: Not for human use. Keep this and all drugs out of reach of children. Antimicrobial drugs, including penicillins and cephalosporins, can cause allergic reactions in sensitized individuals.

To minimize the possibility of allergic reactions, those handling such antimicrobials, including amoxicillin trihydrate/clavulanate potassium, are advised to avoid direct contact of the product with the skin and mucous membranes.

PRECAUTIONS

Prescribing antibacterial drugs in the absence of a proven or strongly suspected bacterial infection is unlikely to provide benefit to treated animals and may increase the risk of the development of drug-resistant animal pathogens. Safety of use in pregnant or breeding animals has not been determined.

ADVERSE REACTIONS

CLAVAMOX CHEWABLE contains a semisynthetic penicillin (amoxicillin) and has the potential for producing allergic reactions. If an allergic reaction occurs, administer epinephrine and/or steroids.

Post-Approval Experience (July, 2017):
The following adverse events are based on post-approval adverse drug experience reporting. Not all adverse events are reported to FDA/CVM. It is not always possible to reliably estimate the adverse event frequency or establish a causal relationship to product exposure using these data. The following adverse events reported for dogs and cats are listed in decreasing order of reporting frequency for CLAVAMOX: Anorexia, lethargy, vomiting and diarrhea.
For a copy of the Safety Data Sheet or to report adverse reactions, call Zoetis Inc. at 1-888-963-8471. For additional information about adverse drug experience reporting for animal drugs, contact FDA at 1-888-FDA-VETS or www.fda.gov/reportanimalae.

ACTIONS

The 2 components are rapidly absorbed resulting in amoxicillin and clavulanic acid concentrations in serum, urine, and tissues similar to those produced when each is administered alone.
Amoxicillin and clavulanic acid diffuse readily into most body tissues and fluids with the exception of brain and spinal fluid, which amoxicillin penetrates adequately when meninges are inflamed. Most of the amoxicillin is excreted unchanged in the urine. Clavulanic acid’s penetration into spinal fluid is unknown at this time. Approximately 15% of the administered dose of clavulanic acid is excreted in the urine within the first 6 hours.
CLAVAMOX CHEWABLE combines the distinctive properties of a broad-spectrum antibiotic and a β-lactamase inhibitor to effectively extend the antibacterial spectrum of amoxicillin to include β-lactamase-producing as well as non-β-lactamase-producing aerobic and anaerobic organisms.

MICROBIOLOGY

Amoxicillin is bactericidal in action and acts through the inhibition of biosynthesis of cell wall mucopeptide of susceptible organisms. The action of clavulanic acid extends the antimicrobial spectrum of amoxicillin to include organisms resistant to amoxicillin and other β-lactam antibiotics. Amoxicillin/clavulanate has been shown to have a wide range of activity which includes β-lactamase-producing strains of both gram-positive and gram-negative aerobes, facultative anaerobes, and obligate anaerobes. Many strains of the following organisms, including β-lactamase-producing strains, isolated from veterinary sources, were found to be susceptible to amoxicillin/ clavulanate in vitro but the clinical significance of this activity has not been demonstrated for some of these organisms in animals.

Aerobic bacteria, including Staphylococcus aureus*, β-lactamase-producing Staphylococcus aureus* (penicillin resistant), Staphylococcus species*, Staphylococcus epidermidis, Staphylococcus intermedius, Streptococcus faecalis, Streptococcus species*, Corynebacterium pyogenes, Corynebacterium species, Erysipelothrix rhusiopathiae, Bordetella bronchiseptica, Escherichia coli*, Proteus mirabilis, Proteus species, Enterobacter species, Klebsiella pneumoniae, Salmonella dublin, Salmonella typhimurium, Pasteurella multocida, Pasteurella hemolytica, Pasteurella species*.

* The susceptibility of these organisms has also been demonstrated in in vivo studies.

Studies have demonstrated that both aerobic and anaerobic flora are isolated from gingival cultures of dogs with clinical evidence of periodontal disease. Both gram-positive and gram-negative aerobic and anaerobic subgingival isolates indicate sensitivity to amoxicillin/ clavulanic acid during antimicrobial susceptibility testing.

SUSCEPTIBILITY TEST

The recommended quantitative disc susceptibility method (FEDERAL REGISTER 37:20527-29; Bauer AW, Kirby WMM, Sherris JC, et al: Antibiotic susceptibility testing by standardized single disc method. Am J Clin Path 45:493, 1966) utilized 30 mcg Augmentin® (AMC) discs for estimating the susceptibility of bacteria to CLAVAMOX CHEWABLE Tablets.

PALATABILITY

The palatability of CLAVAMOX CHEWABLE Tablets was evaluated in a multi-location field trial. One hundred twelve (112) client-owned dogs were dosed with CLAVAMOX CHEWABLE Tablets at 6.25 mg/lb (12.5 mg/kg) twice daily for 7 days and evaluated for palatability of the product. Dogs freely consumed 83% of their doses within 5 minutes of offering from an empty bowl or owner’s hand. Of the 17% of doses unconsumed after 5 minutes, 16% were administered with a treat/food or forced intake and 1% of doses were refused.

STORAGE INFORMATION

Store in a dry, cool place at temperatures not above 25°C (77°F). Do not remove from foil strip until ready to use.

HOW SUPPLIED

CLAVAMOX CHEWABLE Tablets in the following strengths are supplied in single strip rolls containing 112 chewable tablets.

Each 62.5-mg tablet contains amoxicillin trihydrate equivalent to 50 mg of amoxicillin activity and 12.5 mg of clavulanic acid as the potassium salt. For use in dogs and cats.

Each 125-mg tablet contains amoxicillin trihydrate equivalent to 100 mg of amoxicillin activity and 25 mg of clavulanic acid as the potassium salt. For use in dogs only.

Each 250-mg tablet contains amoxicillin trihydrate equivalent to 200 mg of amoxicillin activity and 50 mg of clavulanic acid as the potassium salt. For use in dogs only.

Each 375-mg tablet contains amoxicillin trihydrate equivalent to 300 mg of amoxicillin activity and 75 mg of clavulanic acid as the potassium salt. For use in dogs only.

Dispense according to recommendations outlined in Dosage and Administration section.

Approved by FDA under NADA # 055-099

CLAVAMOX is a trademark owned by and used under license from GlaxoSmithKline.
Augmentin is a trademark owned by GlaxoSmithKline.

Manufactured by:
Haupt Pharma, Latina, Italy

Distributed by:
Zoetis Inc.
Kalamazoo, MI 49007

Revised: September 2020
51745581